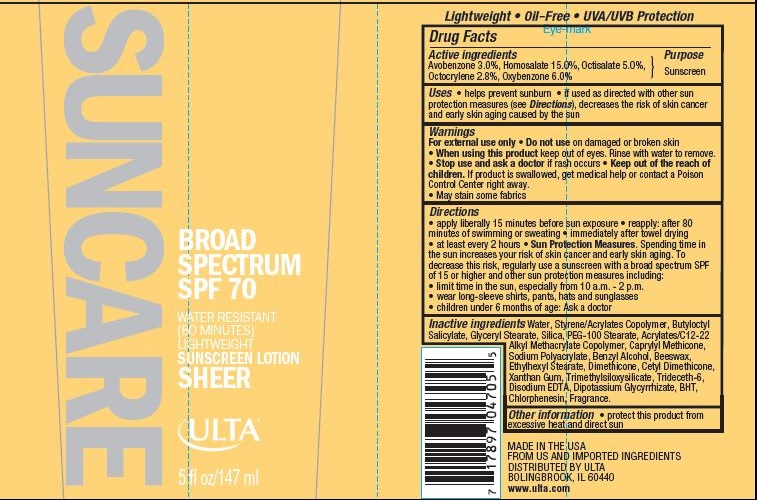 DRUG LABEL: ULTA SUN DRY TOUCH SPF 70
NDC: 62296-8900 | Form: LOTION
Manufacturer: Ulta
Category: otc | Type: HUMAN OTC DRUG LABEL
Date: 20160125

ACTIVE INGREDIENTS: AVOBENZONE 3 g/100 g; HOMOSALATE 15 g/100 g; OCTISALATE 5 g/100 g; OCTOCRYLENE 2.8 g/100 g; OXYBENZONE 6 g/100 g
INACTIVE INGREDIENTS: WATER; BUTYLOCTYL SALICYLATE; SILICON DIOXIDE; GLYCERYL MONOSTEARATE; PEG-100 STEARATE; CAPRYLYL TRISILOXANE; BENZYL ALCOHOL; ETHYLHEXYL STEARATE; YELLOW WAX; DIMETHICONE; CHLORPHENESIN; XANTHAN GUM; TRIDECETH-6; EDETATE DISODIUM; BUTYLATED HYDROXYTOLUENE; GLYCYRRHIZINATE DIPOTASSIUM

Drug Facts

ACTIVE INGREDIENT

AVOBENZONE 3.0%, HOMOSALATE 15.0%, OCTISALATE 5.0%, OCTOCRYLENE 2.8%,

OXYBENZONE 6.0%

Purpose

Sunscreen

Uses

- helps prevent sunburn
- if used as directed with other sun protection measures (see Directions), decreases the risk of skin cancer and early skin aging caused by the sun

WARNINGS

For external use only

Do not use

on damaged or broken skin

When using this product

keep out of eyes. Rinse with water to remove.

Stop use and ask a doctor

if rash occurs

Keep out of the reach of children

If product is swallowed, get medical help or contact a Poison Control Center right away.

- May stain some fabrics

Directions

- apply liberally 15 minutes before sun exposure
- reapply: after 80 minutes of swimming or sweating
- immediately after towel drying
- at least every 2 hours
- Sun Protection Measures: Spending time in the sun increases your risk of skin cancer and early skin aging. To decrease this risk, regularly use a sunscreen with a broad spectrum SPF of 15 or higher and other sun protection measures including:
- limit time in the sun, especially from 10:00 a.m. - 2 p.m.
- wear long-sleeve shirts, pants, hats and sunglasses
- children under 6 months of age: Ask a doctor

Inactive ingredients

Water, Styrene/Acrylates Copolymer, Butyloctyl Salicylate, Silica, Glyceryl Stearate, PEG-100 Stearate, Caprylyl Methicone, Sodium Polyacrylate, Benzyl Alcohol, Acrylates/C12-22 Alkyl Methacrylate Copolymer, Ethylhexyl Stearate, Beeswax, Dimethicone, Chlorphenesin, Cetyl Dimethicone, Xanthan Gum, Trimethylsiloxysilicate, Fragrance, Trideceth-6, Disodium EDTA, BHT, Dipotassium Glycyrrhizate.

Other information

- protect this product from excessive heat and direct sun

Principal Display Panel

62296-8900-4
SUNCARE
BROAD SPECTRUM
SPF 70
WATER RESISTANT

(80 MINUTES)

LIGHT WEIGHT

SUNSCREEN LOTION
SHEER

ULTA

5 fl oz/147 ml